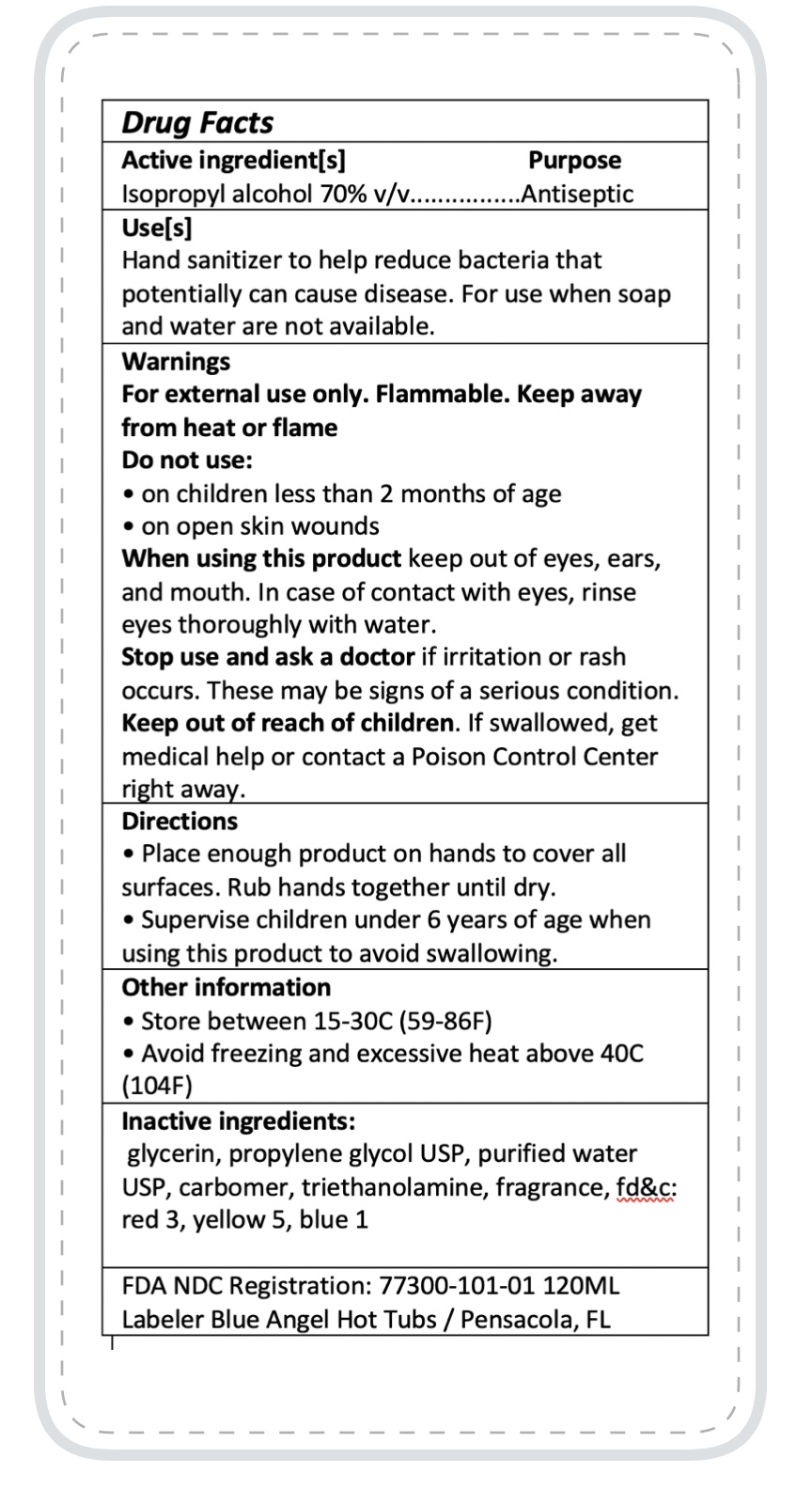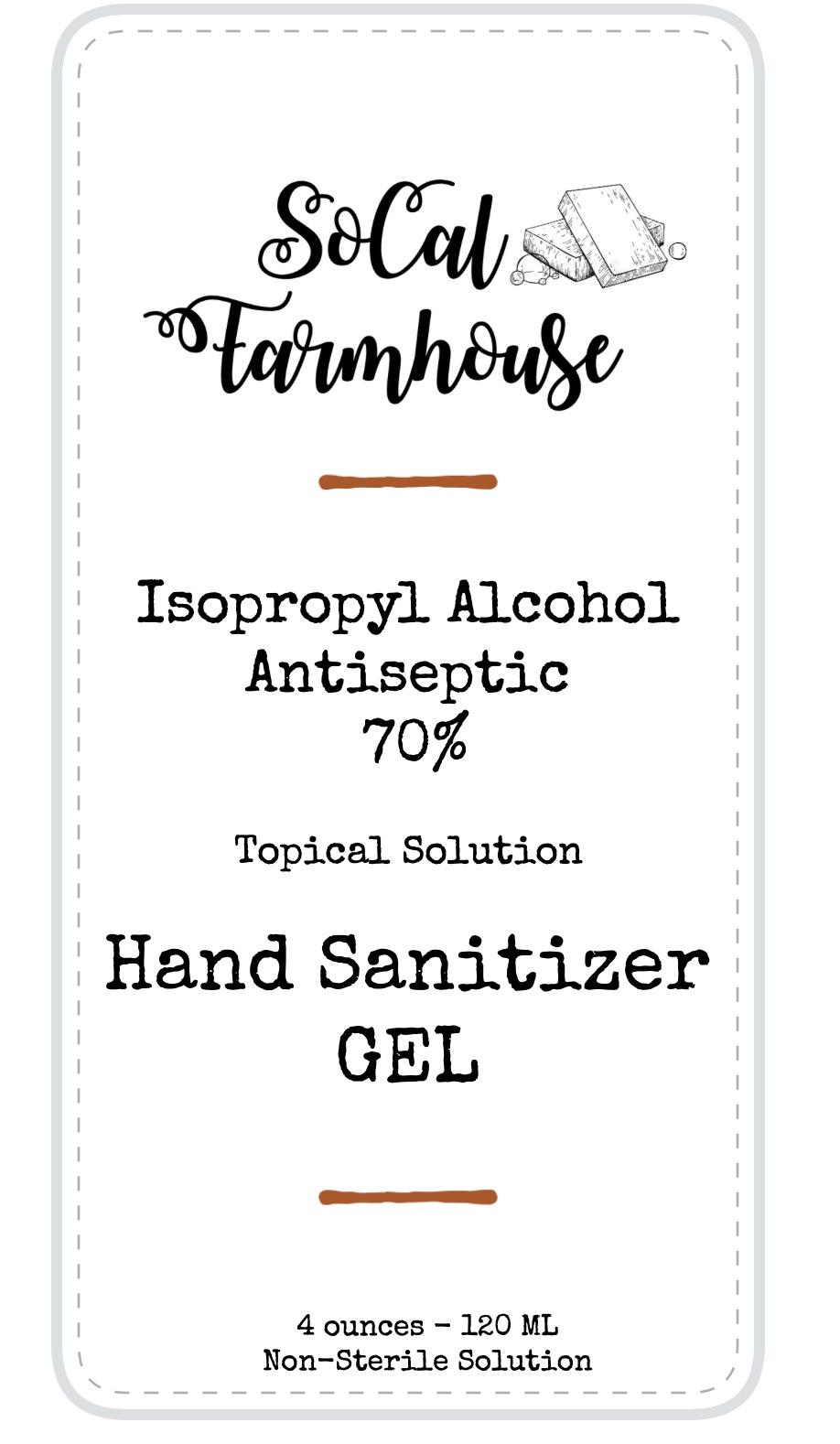 DRUG LABEL: SoCal Farmhouse Gel Hand Sanitizer
NDC: 77300-101 | Form: GEL
Manufacturer: Blue Angel Hot Tubs
Category: otc | Type: HUMAN OTC DRUG LABEL
Date: 20200505

ACTIVE INGREDIENTS: ISOPROPYL ALCOHOL 70 mL/100 mL
INACTIVE INGREDIENTS: GLYCERIN 1.45 mL/100 mL; PROPYLENE GLYCOL 2 mL/100 mL; WATER; FD&C YELLOW NO. 5 0.02 mL/100 mL; CUPRIC BIS(TRIETHANOLAMINE) 3 mL/100 mL; CARBOMER 940 0.3 mL/100 mL; FD&C BLUE NO. 1 0.02 mL/100 mL; FD&C RED NO. 3 0.05 mL/100 mL

SoCal Farmhouse Gel Hand Sanitizer 120 ML

This is a hand sanitizer manufactured according to the Temporary Policy for Preparation of Certain Alcohol-Based Hand Sanitizer Products During the Public Health Emergency (CoViD-19); Guidance for Industry.

Active Ingredient(s)

Isopropyl Alcohol 70% v/v. Purpose: Antiseptic

Purpose

Antiseptic, Hand Sanitizer

Use

Hand Sanitizer to help reduce bacteria that potentially can cause disease. For use when soap and water are not available.

Warnings

For external use only. Flammable. Keep away from heat or flame

Do not use

- in children less than 2 months of age
- on open skin wounds

When using this product keep out of eyes, ears, and mouth. In case of contact with eyes, rinse eyes thoroughly with water.
Stop use and ask a doctor if irritation or rash occurs. These may be signs of a serious condition.
Keep out of reach of children. If swallowed, get medical help or contact a Poison Control Center right away.

Stop use and ask a doctor if irritation or rash occurs. These may be signs of a serious condition.

Keep out of reach of children. If swallowed, get medical help or contact a Poison Control Center right away.

Directions

- Place enough product on hands to cover all surfaces. Rub hands together until dry.
- Supervise children under 6 years of age when using this product to avoid swallowing.

Other information

- Store between 15-30C (59-86F)
- Avoid freezing and excessive heat above 40C (104F)

Inactive ingredients

glycerin, propylene glycol USP, TRIETHANOLAMINE, purified water USP, carbomer, fd&c red 3, yellow 5, blue 1

Package Label - Principal Display Panel

120 ml NDC: 77300-101-01